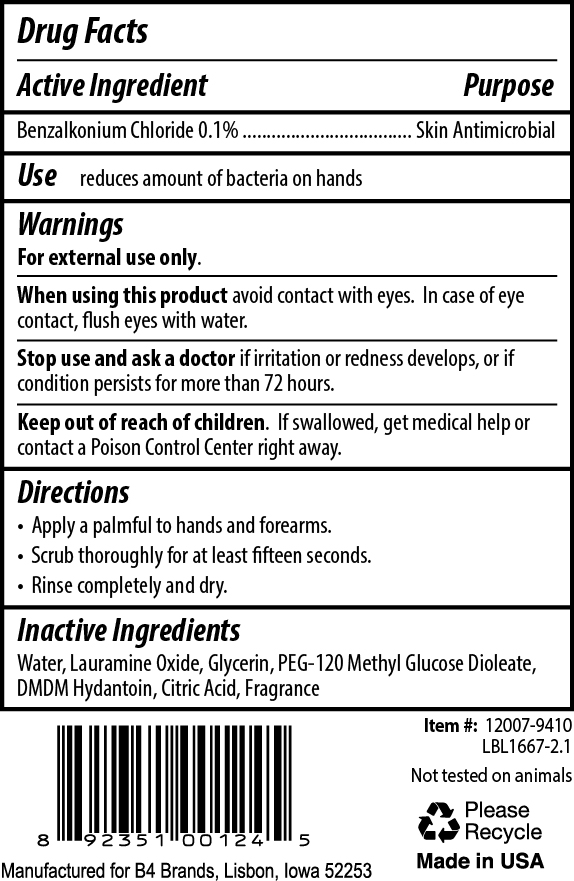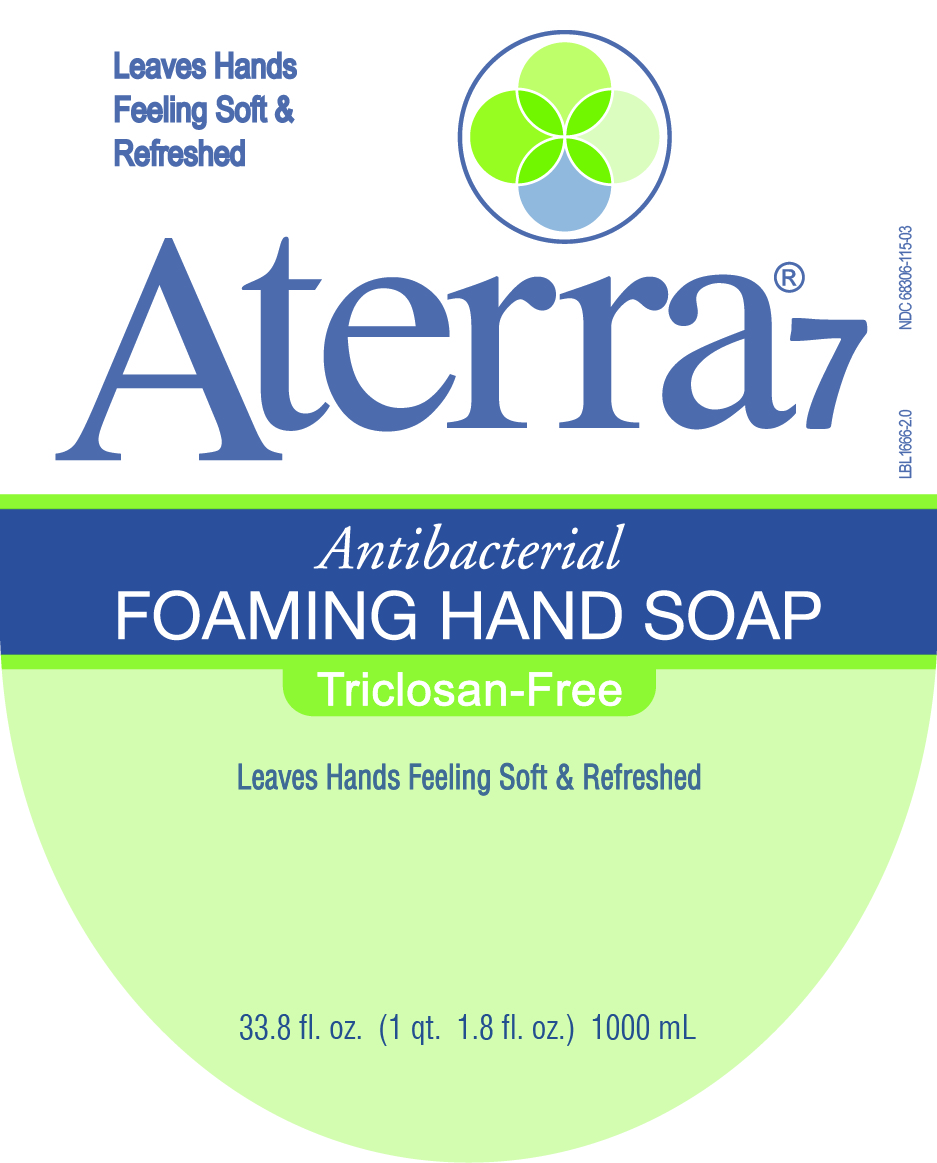 DRUG LABEL: Aterra7 Antibacterial Foaming Hand
NDC: 68306-115 | Form: SOAP
Manufacturer: B4 Ventures LLC
Category: otc | Type: HUMAN OTC DRUG LABEL
Date: 20250115

ACTIVE INGREDIENTS: BENZALKONIUM CHLORIDE 1 mg/1 mL
INACTIVE INGREDIENTS: WATER; LAURAMINE OXIDE; GLYCERIN; PEG-120 METHYL GLUCOSE DIOLEATE; DMDM HYDANTOIN; CITRIC ACID MONOHYDRATE

Aterra7 Antibacterial Foaming Hand Soap

Active Ingredient

Benzalkonium Chloride 0.1%

Purpose

Skin Antimicrobial

Use

reduces amount of bacteria on hands

Warnings

For external use only.

When using this product avoid contact with eyes. In case of eye contact, flush eyes with water.

Stop use and ask a doctorif irritation or redness develops, or if condition persists for more than 72 hours.

Keep out of reach of children. If swallowed, get medical help or contact a Poison Control Center right away.

Directions

- Apply a palmful to hands and forearms.
- Scrub thoroughly for at least 15 seconds.
- Rinse completely and dry.

Inactive Ingredients

Water, Lauramine Oxide, Glycerin, PEG-120 Methyl Glucose Dioleate, DMDM Hydantoin, Citric Acid, Fragrance